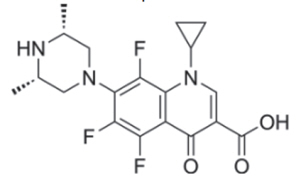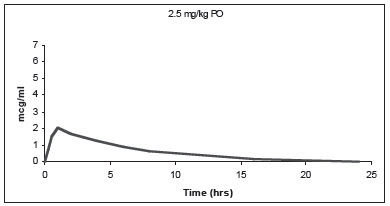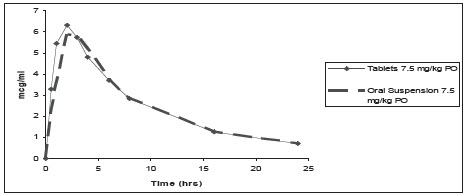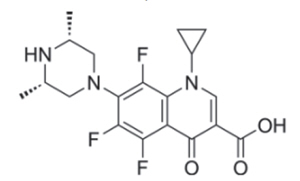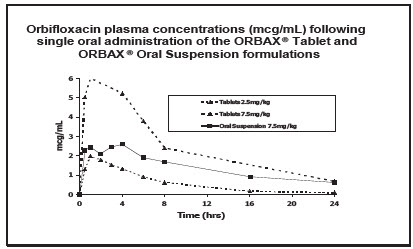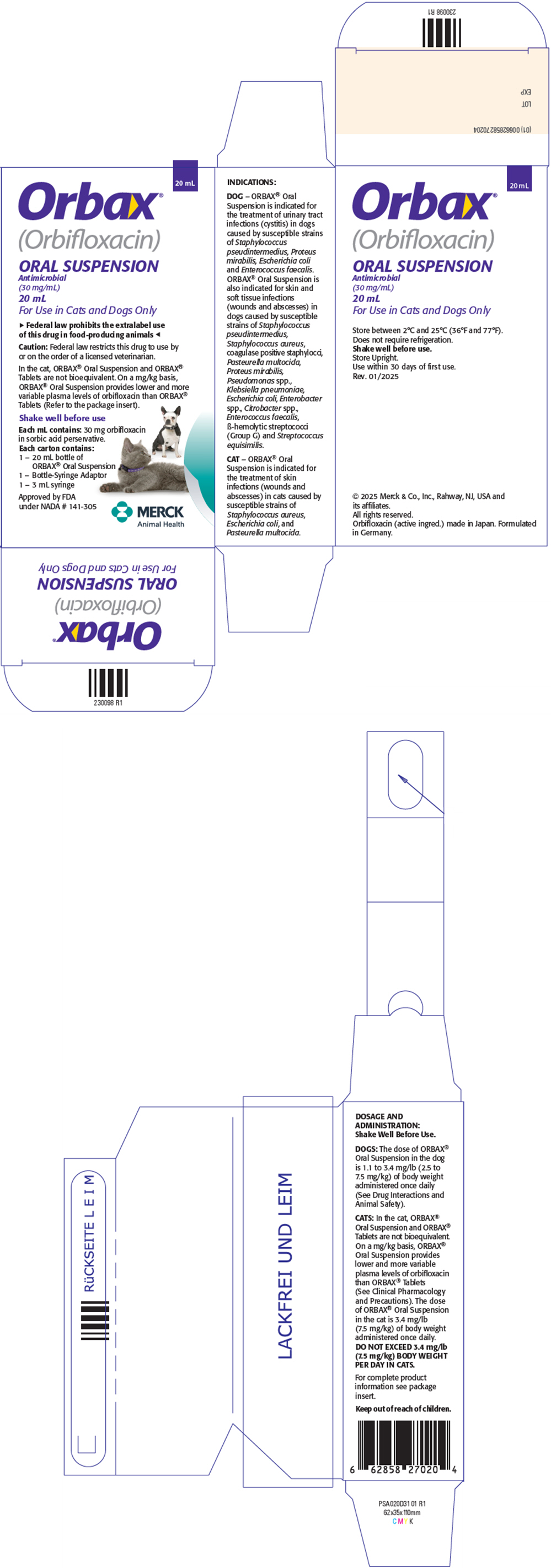 DRUG LABEL: Orbax
NDC: 0061-2321 | Form: SUSPENSION
Manufacturer: Merck Sharp & Dohme Corp.
Category: animal | Type: PRESCRIPTION ANIMAL DRUG LABEL
Date: 20251219

ACTIVE INGREDIENTS: ORBIFLOXACIN 30 mg/1 mL

ORBAX® (Orbifloxacin) Oral Suspension

For Oral Use in Dogs Only.

Approved by FDA under NADA # 141-305

FOOD SAFETY WARNING

▶Federal law prohibits the extralabel use of this drug in food-producing animals◀

CAUTION: Federal law restricts this drug to use by or on the order of a licensed veterinarian.

DESCRIPTION

DESCRIPTION: Orbifloxacin is a synthetic broad-spectrum antibacterial agent from the class of fluoroquinolone carboxylic acid derivatives. Orbifloxacin is the international nonproprietary name for 1-cyclopropyl-5,6,8-trifluoro-1,4-dihydro-7-(cis-3,5-dimethyl-1-piperazinyl)-4-oxoquinoline-3-carboxylic acid. The chemical formula for orbifloxacin is C19H20F3N3O3 and its molecular weight is 395.38.

The compound is slightly soluble in water; however, solubility increases in both acidic and alkaline conditions. The compound has two dissociation constants (pKa's): 5.95 and 9.01.

ORBAX® Oral Suspension is a malt flavored antibiotic suspension containing 30 mg/mL of orbifloxacin and sorbic acid as a preservative.

FIGURE 1. Chemical structure of orbifloxacin

VETERINARY INDICATIONS

INDICATIONS: ORBAX® Oral Suspension is indicated for the treatment of urinary tract infections (cystitis) in dogs caused by susceptible strains of Staphylococcus pseudintermedius, Proteus mirabilis, Escherichia coli and Enterococcus faecalis. ORBAX® Oral Suspension is also indicated for skin and soft tissue infections (wounds and abscesses) in dogs caused by susceptible strains of Staphylococcus pseudintermedius, Staphylococcus aureus, coagulase positive staphylococci, Pasteurella multocida, Proteus mirabilis, Pseudomonas spp., Klebsiella pneumoniae, Escherichia coli, Enterobacter spp., Citrobacter spp., Enterococcus faecalis, β-hemolytic streptococci (Group G) and Streptococcus equisimilis.

DOSAGE AND ADMINISTRATION: Shake Well Before Use. BEFORE INITIAL USE, remove the cap and insert the syringe adaptor by pressing firmly into top of bottle. Insert the syringe tip into the adaptor opening and invert the bottle. Withdraw the required amount of medication with the calibrated syringe. After use, replace cap, leaving adaptor in the bottle, and rinse the syringe with water.

The dose of ORBAX® Oral Suspension in the dog is 1.1 to 3.4 mg/lb (2.5 to 7.5 mg/kg) of body weight administered once daily (See Drug interactions and Animal Safety). The determination of dosage for any particular patient must take into consideration such factors as the severity and nature of the infection, the susceptibility of the causative organism, and the integrity of the patient's host-defense mechanisms. Antibiotic susceptibility of the pathogenic organism(s) should be determined prior to use of this preparation. Therapy with ORBAX® Oral Suspension may be initiated before results of these tests are known. Once results become available, continue with appropriate therapy.

For the treatment of skin infections, ORBAX® Oral Suspension should be given for two (2) to three (3) days beyond the cessation of clinical signs to a maximum of 30 days. For the treatment of urinary tract infections, ORBAX® Oral Suspension should be administered for at least 10 consecutive days. If no improvement is seen within five (5) days, the diagnosis should be re-evaluated and a different course of therapy considered.

CONTRAINDICATIONS

CONTRAINDICATIONS: Orbifloxacin and other quinolones have been shown to cause arthropathy in immature animals of most species tested, the dog being particularly sensitive to this side effect. Orbifloxacin is contraindicated in immature dogs during the rapid growth phase (between 2 and 8 months of age in small and medium-sized breeds, and up to 18 months of age in large and giant breeds).

Orbifloxacin is contraindicated in dogs known to be hypersensitive to quinolones.

WARNINGS

HUMAN WARNING: For use in animals only. Keep out of the reach of children.

Individuals with a history of hypersensitivity to quinolones should avoid this product. In humans, there is a risk of user photosensitization within a few hours after excessive exposure to quinolones. If excessive accidental exposure occurs, avoid direct sunlight.

Avoid contact with eyes. In case of contact, immediately flush eyes with copious amounts of water for 15 minutes. In case of dermal contact, wash skin with soap and water. Consult a physician if irritation persists following ocular or dermal exposure.

PRECAUTIONS

PRECAUTIONS: Prescribing antibacterial drugs in the absence of a proven or strongly suspected bacterial infection is unlikely to provide benefit to treated animals and may increase the risk of the development of drug-resistant animal pathogens.

Administer orbifloxacin with caution in the presence of hepatic insufficiency/impairment. Please refer to the cat side of this package insert for Precautions related specifically to cats. Quinolones should be used with caution in animals with known or suspected central nervous system (CNS) disorders. In such animals, quinolones have, in rare instances, been associated with CNS stimulation, which may lead to convulsive seizures. Quinolones have been shown to produce erosions of cartilage of weight-bearing joints and other signs of arthropathy in immature animals of various species. The safety of orbifloxacin in animals that are used for breeding or that are pregnant and/or lactating has not been demonstrated.

DRUG INTERACTIONS

DRUG INTERACTIONS: Compounds (eg, sucralfate, antacids, and multivitamins) containing divalent and trivalent cations (eg, iron, aluminum, calcium, magnesium, and zinc) may substantially interfere with the absorption of quinolones resulting in a decrease in product bioavailability. Therefore, the concomitant oral administration of quinolones with foods, supplements, or other preparations containing these compounds should be avoided.

The dosage of theophylline should be reduced when used concurrently with fluoroquinolones. Cimetidine has been shown to interfere with the metabolism of fluoroquinolones and should be used with care when used concurrently. Concurrent use of fluoroquinolones with oral cyclosporine is contraindicated. Concurrent administration of fluoroquinolones may increase the action of oral anticoagulants.

ADVERSE REACTIONS

ADVERSE REACTIONS: In a field study, when the tablet formulation of orbifloxacin was administered at 2.5 mg/kg/day, no drug-related adverse reactions were reported. In a foreign field study using the oral suspension at 7.5 mg/kg/day, vomiting was reported for ORBAX® Oral Suspension and the comparator.

Post Approval Experience with ORBAX® (orbifloxacin) Tablets (Rev. 2010): The following adverse events are based on post-approval adverse drug experience reporting with ORBAX® (orbifloxacin) Tablets. Not all adverse reactions are reported to FDA CVM. It is not always possible to reliably estimate the adverse event frequency or establish a causal relationship to product exposure using this data. The following adverse events are listed in decreasing order of reporting frequency:

DOG: Vomiting, convulsions, depression/lethargy, anorexia

For a complete listing of adverse reactions for ORBAX® (orbifloxacin) Tablets reported to the CVM see: http://www.fda.gov/reportanimalae

For technical assistance or to report a suspected adverse reaction call 1-800-224-5318.

CLINICAL PHARMACOLOGY:

PHARMACOKINETICS

Pharmacokinetics in healthy, adult Beagle dogs: In fasted animals, orbifloxacin is rapidly and almost completely absorbed from the gastrointestinal tract following oral administration. The absolute bioavailability (F) of an oral dose is approximately 100%. The effects of concomitant feeding on the absorption of orbifloxacin have not been studied in the dog. Divalent cations are generally known to diminish the absorption of fluoroquinolones. (See DRUG INTERACTIONS.)

Distribution in the Body: Orbifloxacin penetrates into most tissues and body fluids following oral dosing. A summary of the body fluid and tissue drug levels at 3 and 6 hours following dose administration is presented in Table 1. Particularly high levels of orbifloxacin are found in the prostate, kidneys, liver, bile, lungs, lymph nodes, small intestine, cartilage, muscle, salivary gland and testes.

Table 1: Body Fluid/Tissue Distribution of ^14C-Orbifloxacin-derived radioactivity in Dogs following Single and Multiple Oral Dose Administration of 5.0 mg/kg
Post-Treatment Levels of ^14C-Orbifloxacin Derived Radioactivity (μg equiv/g)
 | Single Dose |  | Multiple Dose
 | 3 hours (n=1) | 6 hours (n=1) | 6 hours following the final dose of a once daily for five day regimen (n=1)
Body Fluids
Aqueous humor | . . . | . . . | 0.526
Bile | 151 | 63.9 | 280
Blood | . . . | 1.43 | 1.29
Red Blood Cells | 3.19 | 1.29 | 1.11
Plasma | . . . | . . . | 1.56
Cerebrospinal fluid | 0.203 | 0.300 | 0.548
Tissues
Bone | 0.231 | 0.258 | 0.152
Cartilage | 4.67 | 6.62 | 4.72
Kidneys | 8.89 | 3.83 | 4.28
Liver | 10.1 | 3.49 | 3.30
Lungs | 4.10 | 2.03 | 1.81
Lymph nodes | 6.44 | 2.72 | 2.06
Muscle | 4.55 | 1.94 | 2.21
Prostate | 6.00 | 1.91 | 1.35
Salivary gland | 10.2 | 4.43 | 3.17
Skin | 1.90 | 1.05 | 1.57
Small Intestine | 6.00 | 6.31 | 6.91
Testes | 4.59 | 2.89 | 2.48

In a pharmacokinetic study conducted with ORBAX® (orbifloxacin) Tablets, within 24 hours of administration, approximately 40% of an oral dose was excreted into the urine unchanged in dogs with normal renal function (n=12). This supports the effectiveness of orbifloxacin in the treatment of urinary tract infections. Based on the plasma elimination half-life and the dosing interval, negligible drug accumulation is expected with multiple dosing.

Pharmacokinetic parameters estimated in a randomized two-period, two-sequence crossover study using single intravenous and oral doses are summarized in Tables 2 and 3 and Figure 2.

Table 2: Mean Pharmacokinetic Parameters Estimated in 12 Adult Beagle Dogs After a Single IV Bolus of Orbifloxacin at 2.5 mg/kg
Pharmacokinetic Parameter | Estimate (SE)
Total body clearance (mL/min/kg) | 2.9 ± 0.2
Volume of distribution at steady state, Vss (L/kg) | 1.2 ± 0.2
AUC0-∞ (μg∙h/mL) | 14.3 ± 0.9
Terminal plasma elimination half-life, T½ (hrs) | 5.4 ± 1.1

Table 3: Mean Pharmacokinetic Parameters Estimated in 12 Adult Beagle Dogs After a Single Oral Dose of Orbifloxacin Tablets at 2.5 mg/kg
Pharmacokinetic Parameter | Tablets Estimate (SE)
Total body clearance/F (mL/min/kg) | 3.0 ± 0.2
Maximum concentration Cmax (μg/mL) | 2.3 ± 0.3
Time of maximum concentration, Tmax (minutes) | 46 ± 27
AUC0-∞ (μg∙h/mL) | 14.3 ± 1.4
Terminal plasma elimination half-life, T½ (hrs) | 5.6 ± 1.1

Figure 2: Plasma Concentration of Orbifloxacin (Tablet Formulation) vs. Time in Dogs

Pharmacokinetic parameters estimated in a randomized, two-period, two-sequence crossover biocomparability study between the orally administered ORBAX® (orbifloxacin) Tablets and ORBAX® Oral Suspension are summarized in Table 4 and Figure 3. Results of this study demonstrate that ORBAX® Oral Suspension is bioequivalent to ORBAX® (orbifloxacin) Tablets.

Table 4: Mean Pharmacokinetic Parameters Estimated in 24 Adult Beagle Dogs After a Single Oral Dose of Orbifloxacin Tablets or Oral Suspension at 7.5 mg/kg
Pharmacokinetic Parameter | Tablets Estimate (SE) | Oral Suspension Estimate (SE)
Total body clearance/F (mL/min/kg) | 2.09 ± 0.32 | 2.17 ± 0.54
Maximum concentration Cmax (μg/mL) | 6.32 ± 0.87 | 5.82 ± 0.87
Time of maximum concentration, Tmax (hrs) | 2.02 ± 0.94 | 2.29 ± 0.55
AUC0-∞ (μg∙h/mL) | 60.85 ± 9.08 | 60.37 ± 11.50
Terminal plasma elimination half-life, T½ (hrs) | 6.13 ± 0.88 | 6.26 ± 0.84

FIGURE 3: Mean plasma concentration of orbifloxacin (tablets and oral suspension) vs. time in dogs (7.5 mg/kg)

MICROBIOLOGY

MICROBIOLOGY: Orbifloxacin is bactericidal against a wide range of gram-negative and gram-positive organisms and exerts its antibacterial effect through interference with the bacterial enzyme DNA gyrase which is needed for the maintenance and synthesis of bacterial DNA. The time-kill kinetics of orbifloxacin against Staphylococcus spp. has been described by Ganiere et al., 2004^1.

The minimum inhibitory concentrations (MICs) of pathogens isolated in multicentered clinical field studies performed with the oral tablet formulation in the United States were determined using Clinical and Laboratory Standards Institute (CLSI) guidelines^2, and are in Tables 7 and 8.

Table 7: MIC Values [The correlation between the in vitro susceptibility data (MIC values) and clinical response has not been determined.] (μg/mL) of Orbifloxacin Against Urinary Pathogens Isolated Between 1994 and 1996 From Clinical Infections During Field Studies in Dogs
Bacteria Name | Number of Isolates | MIC50 | MIC90 | MIC Range
Staphylococcus pseudintermedius | 5 | [There were an insufficient number of isolates to calculate the MIC50 or MIC90.] |  | 0.0975 - 0.39
Proteus mirabilis | 19 | 0.78 | 1.56 | 0.048 - 1.56
Escherichia coli | 35 | 0.0975 | 0.39 | 0.024 - ≥25
Enterococcus faecalis | 5 |  |  | 0.003 - 3.12

Table 8: MIC Values [The correlation between the in vitro susceptibility data (MIC values) and clinical response has not been determined.] (μg/mL) of Orbifloxacin Against Skin Pathogens Isolated Between 1994 and 1996 From Clinical Infections During Field Studies in Dogs
Bacteria Name | Number of Isolates | MIC50 | MIC90 | MIC Range
Staphylococcus pseudintermedius | 51 | 0.195 | 0.39 | 0.003 – 1.56
Staphylococcus aureus | 8 | [There were an insufficient number of isolates to calculate the MIC50 or MIC90.] |  | 0.195 - ≥25
coagulase positive staphylococci | 59 | 0.195 | 0.39 | 0.003 - ≥25
Pasteurella multocida | 5 |  | 0 | 0.003 – 0.78
Proteus mirabilis | 7 |  |  | 0.39 – 1.56
Pseudomonas aeruginosa | 14 | 3.125 | 12.5 | 0.39 - ≥25
Pseudomonas spp. | 18 | 3.125 | 12.5 | 0.02 - ≥25
Klebsiella pneumoniae | 9 |  |  | 0.0975 – 0.195
Escherichia coli | 28 | 0.0975 | 0.39 | 0.012 – 6.25
Enterobacter spp. | 24 | 0.0975 | 0.39 | 0.012 - 6.25
Citrobacter spp. | 4 |  |  | 0.024 – 0.0975
Enterococcus faecalis | 11 |  |  | 0.3 - ≥25
β-hemolytic streptococci (Group G) | 22 | 0.39 | 1.56 | 0.006 – 3.12
Streptococcus equisimilis | 10 |  |  | 0.003 – 0.78

EFFECTIVENESS: Clinical effectiveness for ORBAX® (orbifloxacin) Tablets (NADA 141-081) was established for the treatment of skin and soft tissue infections (wounds and abscesses) and urinary tract infections (cystitis) in dogs. Specific bacterial pathogens isolated in the clinical field study are listed in the MICROBIOLOGY section.

Effectiveness of the oral suspension in dogs was established in a biocomparability study demonstrating that ORBAX® Oral Suspension is bioequivalent to ORBAX® (orbifloxacin) Tablets.

ANIMAL SAFETY:

No mortality occurred when ORBAX® Oral Suspension was administered to young, clinically healthy, adult Beagles at doses of 7.5 mg/kg, 22.5 mg/kg, and 37.5 mg/kg once daily for 30 consecutive days, and at 75 mg/kg/day once daily for 10 consecutive days. Body temperature, respiratory rate and heart rate were not affected by orbifloxacin treatment. Discoloration of the feces (white to yellow) was observed at all dose levels. At 37.5 and 75 mg/kg/day, ORBAX® Oral Suspension caused gastrointestinal signs, including emesis and soft and/or mucoid feces. At doses of 75 mg/kg/day, hypersalivation was observed. Male dogs treated with 75 mg/kg/day had reduced food consumption and mild weight loss. Glucosuria and lower urine pH were also observed in 7 out of 10 dogs treated with orbifloxacin at 75 mg/kg/day. No other changes in clinical chemistry related to these changes in the urinalysis were observed. The mechanism responsible for the glucosuria and lower pH in this group could not be determined. Following 10 days of treatment with 75 mg/kg/day, one male dog developed hepatic perilobular necrosis, bile duct hyperplasia and inflammation associated with serum elevations in bilirubin and hepatic enzymes (ALK, ALT, AST, GGT). The dog completed the study without clinical signs of illness. At necropsy, the liver had a tan discoloration and weighed significantly less than the livers from other dogs in the group and control dogs. No treatment-related pathologic liver changes were noted in any other dogs treated with orbifloxacin during the study. Articular cartilage defects in the head of the humerus in one male dog in the 3× dose group, and in the medial condyle of the distal femur in one male dog in the 5× dose group were observed. Based on microscopic examination of these lesions it was determined that both lesions were long standing and were present prior to treatment with orbifloxacin. (See CONTRAINDICATIONS)

PALATABILITY: In a field palatability study, conducted in 81 dogs, ORBAX® Oral Suspension was accepted by 96.3% of the dogs following oral administration.

STORAGE AND HANDLING

STORAGE CONDITIONS: Store between 2°C and 25°C (36°F and 77°F). ORBAX® Oral Suspension does not require refrigeration. Shake well before use. Store upright. Use within 30 days of first use.

HOW SUPPLIED

HOW SUPPLIED: ORBAX® Oral Suspension is supplied in a sealed bottle with a 20 mL deliverable volume.

REFERENCES:

^1 Ganiere JP, Medaille C, and Etoré F: In vitro antimicrobial activity of orbifloxacin against Staphylococcus intermedius isolates from canine skin and ear infections. Research in Veterinary Science 77:67-71, 2004.

^2 CLSI Document M37-A3 Development of In Vitro Susceptibility Testing Criteria and Quality Control Parameters for Veterinary Antimicrobial Agents; Approved Guideline—Third Edition

Formulated in Friesoythe, Germany
Intervet Inc (d/b/a Merck Animal Health)
Rev. 01/2025

© 2025 Merck & Co., Inc., Rahway, NJ, USA and its affiliates.
All rights reserved.

230097 R5

ORBAX® (Orbifloxacin) Oral Suspension

For Oral Use in Cats Only.

Approved by FDA under NADA # 141-305

FOOD SAFETY WARNING

▶Federal law prohibits the extralabel use of this drug in food-producing animals◀

CAUTION: Federal law restricts this drug to use by or on the order of a licensed veterinarian.

DESCRIPTION

DESCRIPTION: Orbifloxacin is a synthetic broad-spectrum antibacterial agent from the class of fluoroquinolone carboxylic acid derivatives. Orbifloxacin is the international nonproprietary name for 1-cyclopropyl-5,6,8-trifluoro-1,4-dihydro-7-(cis-3,5-dimethyl-1-piperazinyl)-4-oxoquinoline-3-carboxylic acid. The chemical formula for orbifloxacin is C19H20F3N3O3 and its molecular weight is 395.38.

The compound is slightly soluble in water; however, solubility increases in both acidic and alkaline conditions. The compound has two dissociation constants (pKa's): 5.95 and 9.01.

ORBAX® Oral Suspension is a malt flavored antibiotic suspension containing 30 mg/mL of orbifloxacin and sorbic acid as a preservative.

FIGURE 1. Chemical structure of orbifloxacin.

VETERINARY INDICATIONS

INDICATIONS: ORBAX® Oral Suspension is indicated for the treatment of skin infections (wounds and abscesses) in cats caused by susceptible strains of Staphylococcus aureus , Escherichia coli , and Pasteurella multocida.

DOSAGE AND ADMINISTRATION: Shake Well Before Use. BEFORE INITIAL USE, remove the cap and insert the syringe adaptor by pressing firmly into top of bottle. Insert the syringe tip into the adaptor opening and invert the bottle. Withdraw the required amount of medication with the calibrated syringe. After use, replace cap, leaving adaptor in the bottle, and rinse the syringe with water.

In the cat, ORBAX® Oral Suspension and ORBAX® (orbifloxacin) Tablets are not bioequivalent. On a mg/kg basis, ORBAX® Oral Suspension provides lower and more variable plasma levels of orbifloxacin than ORBAX® (orbifloxacin) Tablets (See Clinical Pharmacology and Precautions). The dose of ORBAX® Oral Suspension in the cat is 3.4 mg/lb (7.5 mg/kg) of body weight administered once daily. DO NOT EXCEED 3.4 mg/lb (7.5 mg/kg) BODY WEIGHT PER DAY IN CATS. ORBAX® Oral Suspension should be given for two (2) to three (3) days beyond the cessation of clinical signs.

Antibiotic susceptibility of the pathogenic organism(s) should be determined prior to use of this preparation. Therapy with ORBAX® Oral Suspension may be initiated before results of these tests are known. Once results become available, continue with appropriate therapy. If no improvement is seen within 3 to 4 days, the diagnosis should be re-evaluated and a different course of therapy considered.

CONTRAINDICATIONS

CONTRAINDICATIONS: Orbifloxacin and other quinolones have been shown to cause arthropathy in immature animals of most species tested, the dog being particularly sensitive to this side effect. Orbifloxacin is contraindicated in immature dogs during the rapid growth phase (between 2 and 8 months of age in small and medium-sized breeds, and up to 18 months of age in large and giant breeds).

Orbifloxacin is contraindicated in cats known to be hypersensitive to quinolones.

WARNINGS

HUMAN WARNING: For use in animals only. Keep out of the reach of children.

Individuals with a history of hypersensitivity to quinolones should avoid this product. In humans, there is a risk of user photosensitization within a few hours after excessive exposure to quinolones. If excessive accidental exposure occurs, avoid direct sunlight.

Avoid contact with eyes. In case of contact, immediately flush eyes with copious amounts of water for 15 minutes. In case of dermal contact, wash skin with soap and water. Consult a physician if irritation persists following ocular or dermal exposure.

PRECAUTIONS

PRECAUTIONS: Prescribing antibacterial drugs in the absence of a proven or strongly suspected bacterial infection is unlikely to provide benefit to treated animals and may increase the risk of the development of drug-resistant animal pathogens.

The use of fluoroquinolones in cats has been reported to adversely affect the retina. Such products should be used with caution in cats. Blindness has also been reported post-approval in cats. In some cases, blindness has been temporary. DO NOT EXCEED 3.4 mg/lb (7.5 mg/kg) BODY WEIGHT PER DAY IN CATS. If higher blood levels of orbifloxacin are needed, ORBAX® (orbifloxacin) Tablets should be used at a dose of 2.3-3.4 mg/lb (5.0-7.5 mg/kg). On a mg/kg basis, ORBAX® (orbifloxacin) Tablets provide higher and less variable plasma levels of orbifloxacin than ORBAX® Oral Suspension.

Quinolones should be used with caution in animals with known or suspected central nervous system (CNS) disorders. In such animals, quinolones have, in rare instances, been associated with CNS stimulation, which may lead to convulsive seizures. Quinolones have been shown to produce erosions of cartilage of weight-bearing joints and other signs of arthropathy in immature animals of various species. The safety of orbifloxacin in animals that are used for breeding or that are pregnant and/or lactating has not been demonstrated.

DRUG INTERACTIONS

DRUG INTERACTIONS: Compounds (eg, sucralfate, antacids, and multivitamins) containing divalent and trivalent cations (eg, iron, aluminum, calcium, magnesium, and zinc) may substantially interfere with the absorption of quinolones resulting in a decrease in product bioavailability. Therefore, the concomitant oral administration of quinolones with foods, supplements, or other preparations containing these compounds should be avoided.

The dosage of theophylline should be reduced when used concurrently with fluoroquinolones. Cimetidine has been shown to interfere with the metabolism of fluoroquinolones and should be used with care when used concurrently. Concurrent use of fluoroquinolones with oral cyclosporine is contraindicated. Concurrent administration of fluoroquinolones may increase the action of oral anticoagulants.

ADVERSE REACTIONS

ADVERSE REACTIONS: In a field study, when the tablet formulation of orbifloxacin was administered at 2.5 mg/kg/day, no drug-related adverse reactions were reported. In a foreign field study using the oral suspension at 7.5 mg/kg/day, vomiting was reported for ORBAX® Oral Suspension and the comparator.

Post Approval Experience with ORBAX® (orbifloxacin) Tablets (Rev. 2010): The following adverse events are based on post-approval adverse drug experience reporting with ORBAX® Tablets. Not all adverse reactions are reported to FDA CVM. It is not always possible to reliably estimate the adverse event frequency or establish a causal relationship to product exposure using this data. The following adverse events are listed in decreasing order of reporting frequency:

CAT: Blindness, mydriasis, anorexia, ataxia, depression/lethargy, vomiting, convulsions, abnormal retina, hypersalivation. In some cases, blindness has been temporary.

For a complete listing of adverse reactions for ORBAX® (orbifloxacin) Tablets reported to the CVM see: http://www.fda.gov/reportanimalae

For technical assistance or to report a suspected adverse reaction call 1-800-224-5318.

CLINICAL PHARMACOLOGY:

Comparison to ORBAX® (orbifloxacin) Tablets: In the cat, ORBAX® Oral Suspension and ORBAX® (orbifloxacin) Tablets are not bioequivalent. On a mg/kg basis, ORBAX® Oral Suspension provides lower and more variable plasma levels of orbifloxacin than ORBAX® (orbifloxacin) Tablets. When ORBAX® Oral Suspension is dosed at its clinical dose of 7.5 mg/kg, plasma levels of orbifloxacin are consistently higher than those provided by ORBAX® (orbifloxacin) Tablets dosed at the low end (2.5 mg/kg) of its clinical dose range of 2.5 – 7.5 mg/kg. See Figure 2.

Figure 2. Plasma Concentration of Orbifloxacin

Based upon the data generated across three separate studies, the pharmacokinetics of orbifloxacin when administered as a 7.5 mg/kg dose of ORBAX® Oral Suspension is provided in Table 1.

Table 1. Pharmacokinetic parameter estimates following a single 7.5 mg/kg dose of ORBAX® Oral Suspension to Fasted Cats (n=42)
 | AUC 0-24 (µg*hr /mL) |  | Cmax (µg /mL) |  | AUC 0-inf (µg*hr /mL) |  | T 1/2 (hr)
 | Total | Unbound | Total | Unbound | Total | Unbound
Mean | 28.49 | 23.36 | 3.01 | 2.47 | 33.98 | 27.86 | 7.57
Stdev | 9.03 |  | 1.16 |  | 11.37 |  | 3.19
%CV | 31.70 |  | 38.58 |  | 33.47 |  | 42.12

Effect of Food: In the cat, the Cmax and T1/2 of orbifloxacin in plasma is unchanged by concomitant administration of ORBAX® Oral Suspension with food, although the Tmax is delayed and the AUC is increased by an average of 32% (the observed fed/fasted ratios of AUC0-inf values ranged from 0.70 to 1.60).

Plasma Protein-Binding: Orbifloxacin has low protein binding (~18%) in feline plasma.

MICROBIOLOGY

MICROBIOLOGY: Orbifloxacin is bactericidal against a wide range of gram-negative and gram-positive organisms and exerts its antibacterial effect through interference with the bacterial enzyme DNA gyrase which is needed for the maintenance and synthesis of bacterial DNA. The time-kill kinetics of orbifloxacin against Staphylococcus spp. has been described by Ganiere et al., 2004 ^1.

The minimum inhibitory concentrations (MICs) of pathogens isolated in multicentered clinical field study performed with the oral tablet formulation in the United States were determined using Clinical and laboratory Standards Institute (CLSI) guidelines ^2, and are shown in Table 2.

Table 2: MIC Values [The correlation between the in vitro susceptibility data (MIC values) and clinical response has not been determined.] (mcg/mL) of Orbifloxacin Against Skin Pathogens Isolated Between 1994 and 1996 From the ORBAX® Tablet Field Study in Cats
Bacteria Name | Number of Isolates | MIC50 | MIC90 | MIC Range
Staphylococcus aureus | 7 | [There were an insufficient number of isolates to calculate the MIC50 or MIC90.] |  | 0.195-0.39
Pasteurella multocida | 47 | 0.012 | 0.048 | 0.003-0.195
Escherichia coli | 17 | 0.048 | 0.195 | 0.024-25

EFFECTIVENESS: Clinical effectiveness for ORBAX® (orbifloxacin) Tablets (NADA 141-081) was established for the treatment of skin infections (wounds and abscesses) caused by susceptible strains of Pasteurella multocida , Escherichia coli and Staphylococcus aureu in cats. Specific bacterial pathogens isolated in clinical field study are listed in the MICROBIOLOGY section.

Effectiveness of the oral suspension in cats was established through comparison of the plasma pharmacokinetics of the approved product, ORBAX® (orbifloxacin) Tablets (NADA #141-081) to the pharmacokinetics of ORBAX® Oral Suspension. When administered at a dose of 3.4 mg/lb (7.5 mg/kg), ORBAX® Oral Suspension achieves plasma concentrations that exceed those reached following administration of the low end of the approved tablet dose range (2.5 mg/kg). The pharmacokinetic/pharmacodynamic data indicate that cats treated with ORBAX® Oral Suspension at a dose of 3.4 mg/lb (7.5 mg/kg) would exceed the CLSI^2 criterion for clinical success in cats for Pasteurella multocida , Escherichia coli and Staphylococcus aureus with a high degree of certainty on the first and subsequent days of dosing even if it were assumed that all orbifloxacin bound to plasma protein (18%) was biologically unavailable.

ANIMAL SAFETY: Orbifloxacin administered as ORBAX® Oral Suspension to young, clinically healthy, adult cats at doses of 7.5 mg/kg, 15 mg/kg, 45 mg/kg, and 75 mg/kg once daily for 30 consecutive days. At the 45 mg/kg/day and 75 mg/kg/day doses, ORBAX® Oral Suspension caused mild gastrointestinal effects including an increased incidence of emesis, salivation, increased lacrimation and soft, mucoid, and/or watery feces. A mild decrease in food consumption was noted in females that received 45 mg/kg/day and in both sexes that received 75 mg/kg/day.

One cat in the 75 mg/kg/day group had a transient increase in AST (56U/L: normal 14-30) and ALT (642 U/L: normal 42-86) on Day 21 which returned to normal levels by study completion. Additionally at 75 mg/kg/day a decrease in serum alkaline phosphatase was observed in 4 of the 8 cats. Decreased serum albumin was noted in a cat that received 45 mg/kg/day and one cat that received 75 mg/kg/day, with a secondary decrease in serum calcium noted in one cat that received 75 mg/kg/day. Leukocytosis with neutrophilia was seen in one 75 mg/kg/day and two 15 mg/kg/day cats. A marked leukopenia was seen in one cat receiving 15 mg/kg/day.

In cats treated with 45 and 75 mg/kg/day, ophthalmic changes were apparent. Ophthalmologic examinations of multiple cats that received 45 and 75 mg/kg/day revealed tapetal hyperreflectivity, which correlated histopathologically with minimal photoreceptor swelling. Electron microscopy revealed swollen rod cells with disorganized disc material in the outer photoreceptor segments. The ophthalmologic examinations on study Days 24 and 31 revealed test article-related hyperreflectivity (retinal degeneration) in some cats at both 45 and 75 mg/kg/day, although electroretinographic responses at the same time intervals did not indicate any changes in retinal function. Minimal photoreceptor degeneration was noted microscopically in all cats at 45 and 75 mg/kg/day. In the 7.5 mg/kg/day-dose group, two cats had abnormal retinal exams (metallic sheen to tapetum) but no functional or structural pathology was observed.

PALATABILITY: In a field palatability study, conducted in 101 cats, ORBAX® Oral Suspension was accepted by 95% of cats.

STORAGE AND HANDLING

STORAGE CONDITIONS: Store between 2°C and 25°C (36°F and 77°F). ORBAX® Oral Suspension does not require refrigeration. Shake well before use. Store upright. Use within 30 days of first use.

HOW SUPPLIED

HOW SUPPLIED: ORBAX® Oral Suspension is supplied in a sealed bottle with a 20 mL deliverable volume.

REFERENCES:

^1 Ganiere JP, Medaille C, and Etoré F: In vitro antimicrobial activity of orbifloxacin against Staphylococcus intermedius isolates from canine skin and ear infections. Research in Veterinary Science 77:67-71, 2004.

^2 CLSI Document M37-A3 Development of In Vitro Susceptibility Testing Criteria and Quality Control Parameters for Veterinary Antimicrobial Agents; Approved Guideline—Third Edition

Formulated in Friesoythe, Germany
Intervet Inc (d/b/a Merck Animal Health)

Rev. -1/2025

©2025 Merck & Co., Inc., Rahway, NJ USA and its affiliates.
All rights reserved.

230097 R5

PRINCIPAL DISPLAY PANEL - 20 mL Bottle Carton

20 mL

Orbax®
(Orbifloxacin)

ORAL SUSPENSION

Antimicrobial
(30 mg/mL)

20 mL

For Use in Cats and Dogs Only

▶ Federal law prohibits the extralabel use
of this drug in food-producing animals ◀

Caution: Federal law restricts this drug to use by
or on the order of a licensed veterinarian.

In the cat, ORBAX® Oral Suspension and ORBAX®
Tablets are not bioequivalent. On a mg/kg basis,
ORBAX® Oral Suspension provides lower and more
variable plasma levels of orbifloxacin than ORBAX®
Tablets (Refer to the package insert).

Shake well before use

Each mL contains: 30 mg orbifloxacin
in sorbic acid perservative.

Each carton contains:
1 – 20 mL bottle of
ORBAX® Oral Suspension
1 – Bottle-Syringe Adaptor
1 – 3 mL syringe

Approved by FDA
under NADA # 141-305

MERCK
Animal Health